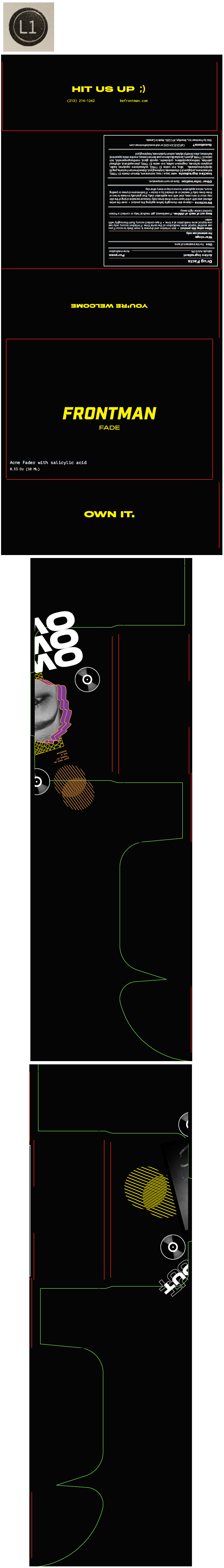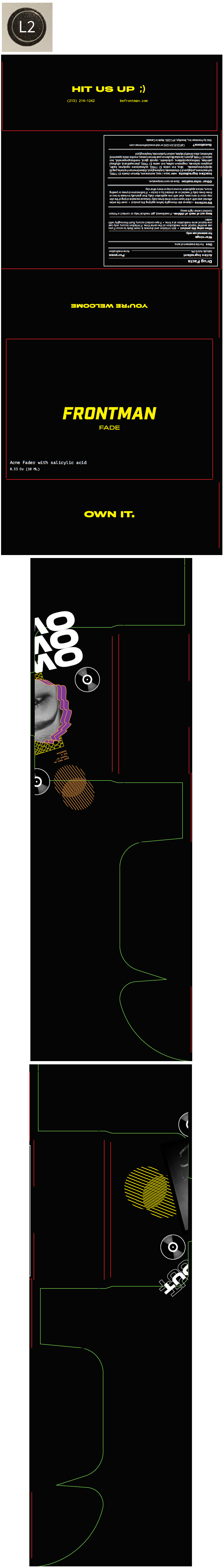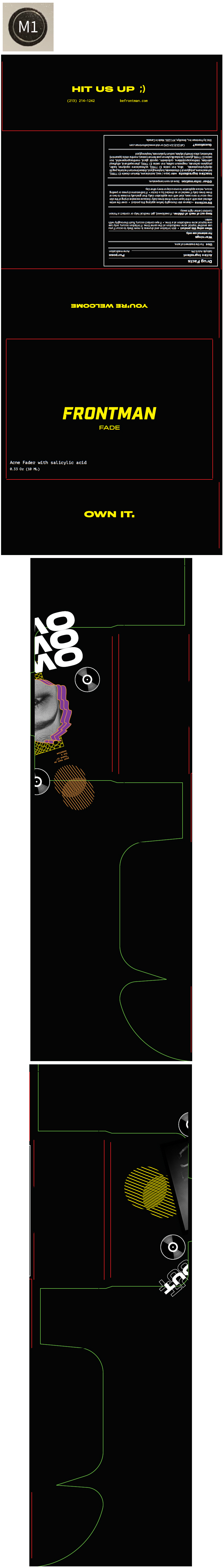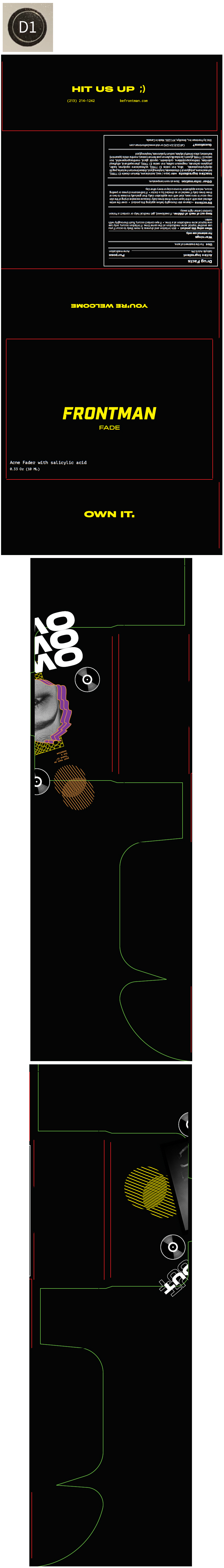 DRUG LABEL: FRONTMAN FADE
NDC: 79638-587 | Form: CREAM, AUGMENTED
Manufacturer: Wingman Cover LLC
Category: otc | Type: HUMAN OTC DRUG LABEL
Date: 20201117

ACTIVE INGREDIENTS: SALICYLIC ACID 5 mg/1 mL
INACTIVE INGREDIENTS: water; isododecane; titanium dioxide; isohexadecane; polyglyceryl-3 diisostearate; butylene glycol; disteardimonium hectorite; peg-30 dipolyhydroxystearate (4000 mw); silicon dioxide; ferric oxide yellow; vinylpyrrolidone/hexadecene copolymer; kaolin; propylene carbonate; magnesium sulfate, unspecified form; ferric oxide red; phenoxyethanol; ethylhexyl palmitate; triethoxycaprylylsilane; caprylyl glycol; 3-((l-menthyl)oxy)propane-1,2-diol; ferrosoferric oxide; glycerin; spearmint; silica dimethyl silylate; hyaluronate sodium; hexylene glycol

FRONTMAN FADE

Drug Facts

Active Ingredient

Salicylic Acid 0.5%

Purpose

Acne medication

Use

For the treatment of acne.

Warnings

For external use only.

When using this product

- skin irritation and dryness is more likely to occur if you use another topical acne medication at the same time. If irritation occurs, only use one topical acne medication at a time.
- If eye contact occurs, flush thoroughly with water.

Keep out of reach of children. If swallowed, get medical help or contact a Poison Control Center right away.

Directions

- cleanse skin thoroughly before applying this product
- cover the entire affected area with a thin layer one to three times daily
- because excessive drying of the skin may occur in rare cases, start with one application daily, then gradually increase to two or three times daily if needed or as directed by a doctor
- if bothersome dryness or peeling occurs, reduce application to once a day or every other day.

Other information

Store at room temperature.

Inactive ingredients

water (aqua / eau), isododecane, titanium dioxide (CI 77891), isohexadecane, polyglyceryl-3 diisostearate, butylene glycol, disteardimonium hectorite, peg-30 dipolyhydroxystearate, silica, iron oxides (CI 77492), vp/hexadecene copolymer, kaolin, propylene carbonate, magnesium sulfate, iron oxides (CI 77491), phenoxyethanol, ethylhexyl palmitate, triethoxycaprylylsilane, cyclodextrin, caprylyl glycol, menthoxypropanediol, iron oxides (CI 77499), glycerin, lactobacillus/lemon peel ferment extract, mentha viridis (spearmint) leaf extract, silica dimethyl silylate, sodium hyaluronate, hexylene glycol

Questions?

Call (213) 214-1242 or visit www.befrontman.com

Dist. by Frontman Inc., Brooklyn, NY 11201. Made in Canada.

PRINCIPAL DISPLAY PANEL - 10 ML Tube Carton - NDC 79638-587-01

FRONTMAN
FADE

Acne Fader with salicylic acid
0.33 Oz (10 ML)

PRINCIPAL DISPLAY PANEL - 10 ML Tube Carton - NDC 79638-588-01

FRONTMAN
FADE

Acne Fader with salicylic acid
0.33 Oz (10 ML)

PRINCIPAL DISPLAY PANEL - 10 ML Tube Carton - NDC 79638-589-01

FRONTMAN
FADE

Acne Fader with salicylic acid
0.33 Oz (10 ML)

PRINCIPAL DISPLAY PANEL - 10 ML Tube Carton - NDC 79638-590-01

FRONTMAN
FADE

Acne Fader with salicylic acid
0.33 Oz (10 ML)